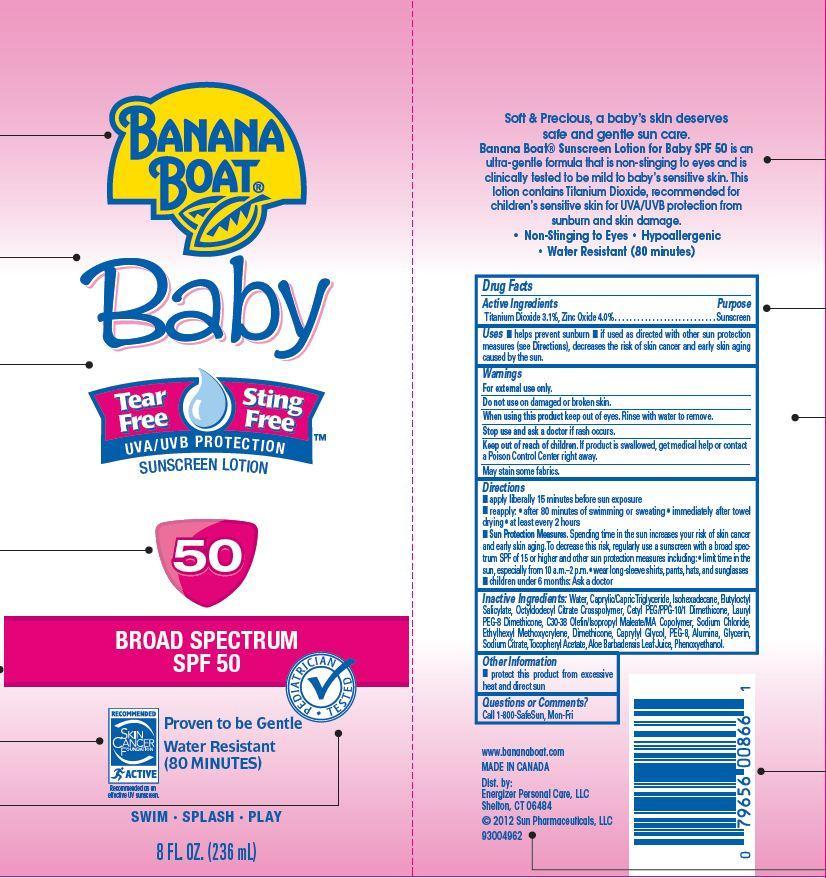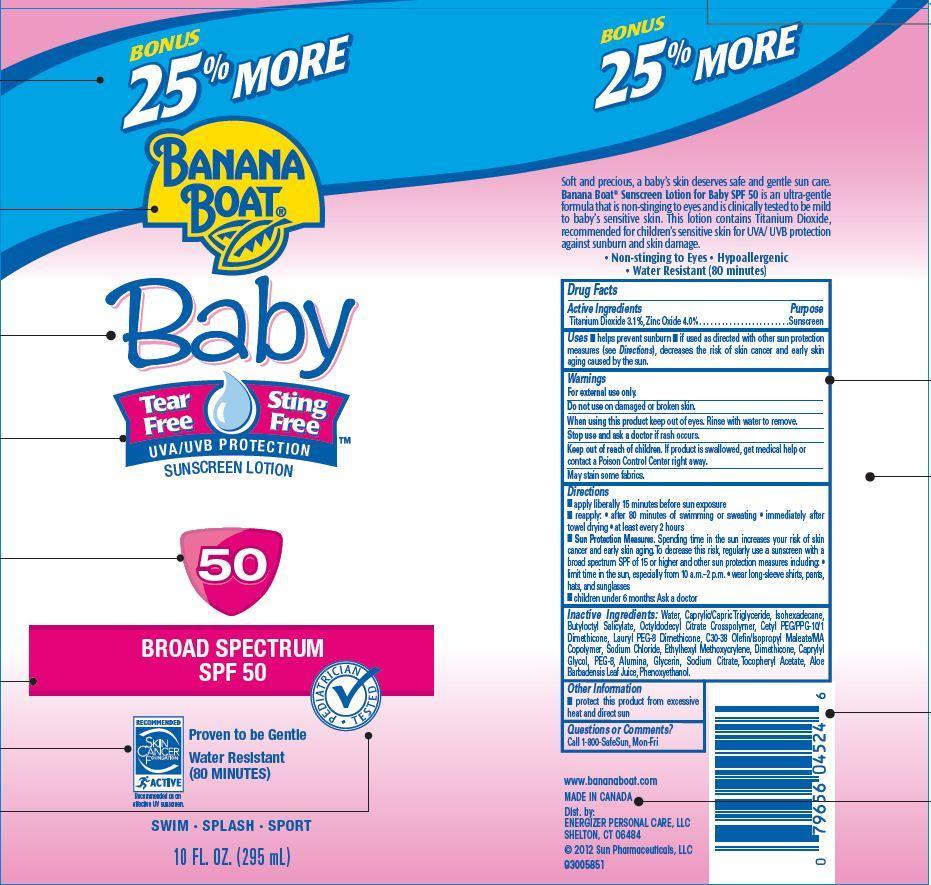 DRUG LABEL: BANANA BOAT
NDC: 63354-050 | Form: LOTION
Manufacturer: Energizer Personal Care LLC
Category: prescription | Type: HUMAN PRESCRIPTION DRUG LABEL
Date: 20121003

ACTIVE INGREDIENTS: TITANIUM DIOXIDE 3.1 g/100 g; ZINC OXIDE 4 g/100 g
INACTIVE INGREDIENTS: WATER; MEDIUM-CHAIN TRIGLYCERIDES; ISOHEXADECANE; BUTYLOCTYL SALICYLATE; CETYL PEG/PPG-10/1 DIMETHICONE (HLB 1.5); SODIUM CHLORIDE; ETHYLHEXYL METHOXYCRYLENE; DIMETHICONE; CAPRYLYL GLYCOL; POLYETHYLENE GLYCOL 400; ALUMINUM OXIDE; GLYCERIN; SODIUM CITRATE; .ALPHA.-TOCOPHEROL ACETATE; ALOE VERA LEAF; PHENOXYETHANOL

Drug Facts

Active Ingredients

Titanium Dioxide 3.1%
Zinc Oxide 4.0%

Purpose

Sunscreen

Uses

- helps prevent sunburn
- if used as directed wiht other sun protection measures (see Directions), decreases the risk of skin cancer and early skin aging caused by the sun.

Warnings

- For external use only
- Do not use on damaged or broken skin

When using this product

keep out of eyes. Rinse with water to remove.

Stop use and ask a doctor

if rash occurs

Keep out of reach of children.

If swallowed, get medical help or contact a Poison Control Center right away.

May stain some fabrics.

Directions

- apply liberally 15 minutes before sun exposure
- reapply
- after 80 minutes of swimming or sweating
- immediately after towel drying
- at least every 2 hours
- Sun Protection Measures: Spending time in the sun increases your risk of skin cancer and early skin aging. To decrease this risk, regulatory use a sunscreen with a broad spectrum SPF of 15 or higher and other sun protection measures including:
- limit time in the sun, especially from 10 a.m.-2 p.m.
- wear long-sleeve shirts, pants, hats, and sunglasses
- children under 6 months: Ask a doctor

Other information

- protect this product from excessive heat and direct sun

Questions or Comments?

Call 1-800-SafeSun, Mon-Fri

Principal Display Panel

Banana Boat

Baby

Tear Free Sting Free

UVA/UVB Protection

Sunscreen Lotion

50

Broad Spectrum SPF 50

Pediatrician Tested

Proven to be Gentle

Water Resistant (80 minutes)

Recommended Skin Cancer Foundation

Active

Recommended as an effective UV sunscreen

Swim Splash Play

8 FL. OZ. (236 mL)

Bonus 25% More

Banana Boat

Baby

Tear Free Sting Free

UVA/UVB Protection

Sunscreen Lotion

50

Broad Spectrum SPF 50

Pediatrician Tested

Proven to be Gentle

Water Resistant (80 minutes)

Recommended Skin Cancer Foundation

Active

Recommended as an effective UV sunscreen

Swim Splash Play

10 FL. OZ. (295 mL)